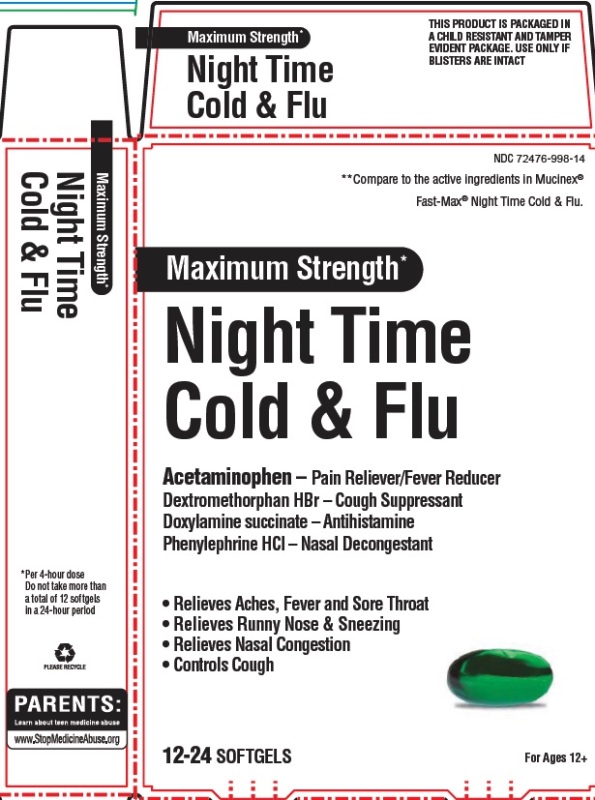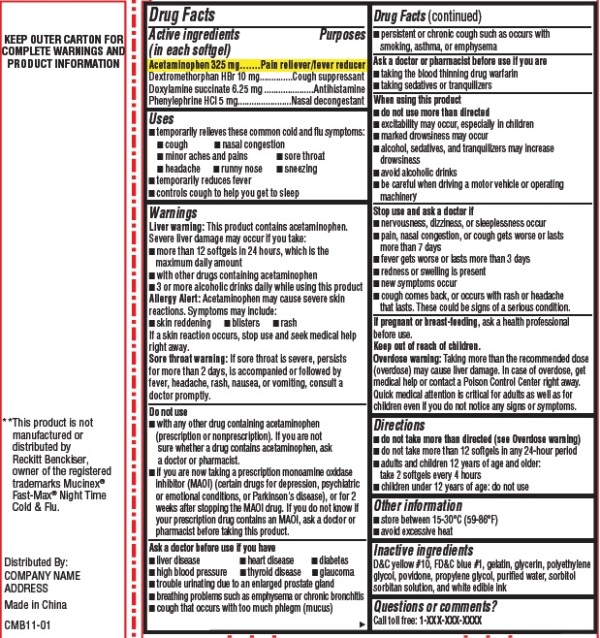 DRUG LABEL: Night Time Cold and Flu
NDC: 72476-998 | Form: CAPSULE, LIQUID FILLED
Manufacturer: Retail Business Services, LLC
Category: otc | Type: HUMAN OTC DRUG LABEL
Date: 20241121

ACTIVE INGREDIENTS: ACETAMINOPHEN 325 mg/1 1; DEXTROMETHORPHAN HYDROBROMIDE 10 mg/1 1; DOXYLAMINE SUCCINATE 6.25 mg/1 1; PHENYLEPHRINE HYDROCHLORIDE 5 mg/1 1
INACTIVE INGREDIENTS: D&C YELLOW NO. 10; FD&C BLUE NO. 1; GELATIN; GLYCERIN; POLYETHYLENE GLYCOL; POVIDONE; PROPYLENE GLYCOL; WATER; SORBITOL; SORBITAN

Night Time Cold & Flu

Drug Facts

Active ingredient (in each softgel)

Acetaminophen 325 mg

Dextromethorphan HBr 10 mg

Doxylamine succinate 6.25 mg

Phenylephrine HCl 5 mg

Purposes

Pain reliever/fever reducer

Cough suppressant

Antihistamine

Nasal decongestant

Uses

- temporarily relieves these common cold and flu symptoms:
- cough
- nasal congestion
- minor aches and pains
- sore throat
- headache
- runny nose
- sneezing
- temporarily reduces fever
- controls cough to help you get to sleep

Warnings

Liver warningThis product contains acetaminophen. Severe liver damage may occur if you take
• more than 4 doses in 24 hrs, which is the maximum daily amount for this product
• with other drugs containing acetaminophen
• 3 or more alcoholic drinks every day while using this product

Allergy alert:Acetaminophen may cause severe skin reactions. Symptoms may include:
• skin reddening
• blisters
• rash

If a skin reaction occurs, stop use and seek medical help right away.

Sore throat warning

If sore throat is severe, persists for more than 2 days, is accompanied or followed by fever, headache, rash, nausea, or vomiting, consult a doctor promptly.

Do not use

- with any other drug containing acetaminophen (prescription or nonprescription). If you are not sure whether a drug contains acetaminophen, ask a doctor or pharmacist.
- if you are now taking a prescription monoamine oxidase inhibitor (MAOI) (certain drugs for depression, psychiatric, or emotional conditions, or Parkinson's disease), or for 2 weeks after stopping the MAOI drug. If you do not know if your prescription drug contains an MAOI, ask a doctor or pharmacist before taking this product.

Ask a doctor before use if you have

- liver disease
- heart disease
- diabetes
- high blood pressure
- thyroid disease
- glaucoma
- trouble urinating due to an enlarged prostate gland
- breathing problems such as emphysema or chronic bronchitis
- cough that occurs with too much phlegm (mucus)
- persistent or chronic cough such as occurs with smoking, asthma, or emphysema

Ask a doctor or pharmacist before use if you are

- taking the blood thinning drug warfarin
- taking sedatives or tranquilizers

When using this product

- do not use more than directed
- excitability may occur, especially in children
- marked drowsiness may occur
- alcohol, sedatives, and tranquilizers may increase drowsiness
- avoid alcoholic drinks
- be careful when driving a motor vehicle or operating machinery

Stop use and ask a doctor if

- nervousness, dizziness, or sleeplessness occur
- pain, nasal congestion, or cough gets worse or lasts more than 7 days
- fever gets worse or lasts more than 3 days
- redness or swelling is present
- new symptoms occur
- cough comes back, or occurs with rash or headache that lasts. These could be signs of a serious condition.

PREGNANCY OR BREAST FEEDING

If pregnant or breast-feeding,ask a health professional before use.

Keep out of reach of children.

Overdose warning

Taking more than the recommended dose (overdose) may cause liver damage. In case of overdose, get medical help or contact a Poison Control Center right away. Quick medical attention is critical for adults as well as for children even if you do not notice any signs or symptoms.

Directions

- do not take more than directed (see Overdose warning)
- do not take more than 12 softgels in any 24-hour period
- adults and children 12 years of age and older: take 2 softgels every 4 hours
- children under 12 years of age: do not use

Other information

- store between 15-30°C (59-86°F)
- avoid excessive heat

Inactive ingredient

D&C yellow #10, FD&C blue #1, gelatin, glycerin, polyethylene glycol, povidone, propylene glycol, purified water, sorbitol sorbitan solution, and white edible ink

Questions or Comments?

Call toll free: 1-866-322-2439

PRINCIPAL DISPLAY PANEL

CareOne Nighttime Cold & Flu 16ct

compare to Mucinex Fast-Max Night Time Cold & Flu active ingredients

NDC 72476-998-14